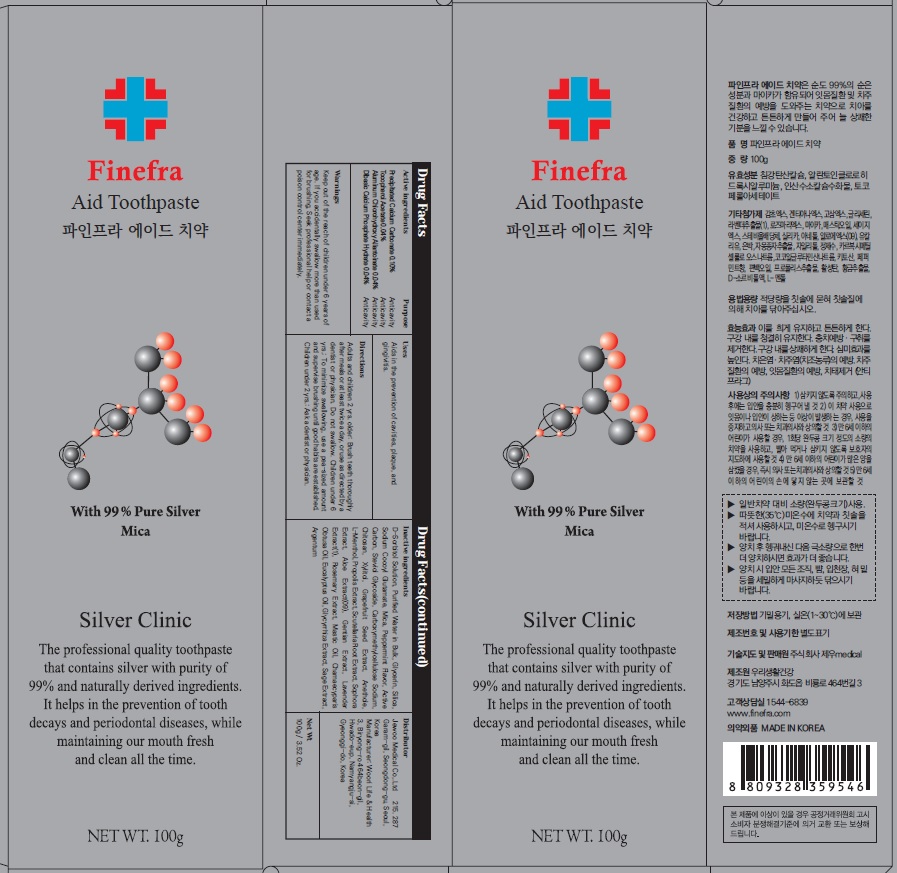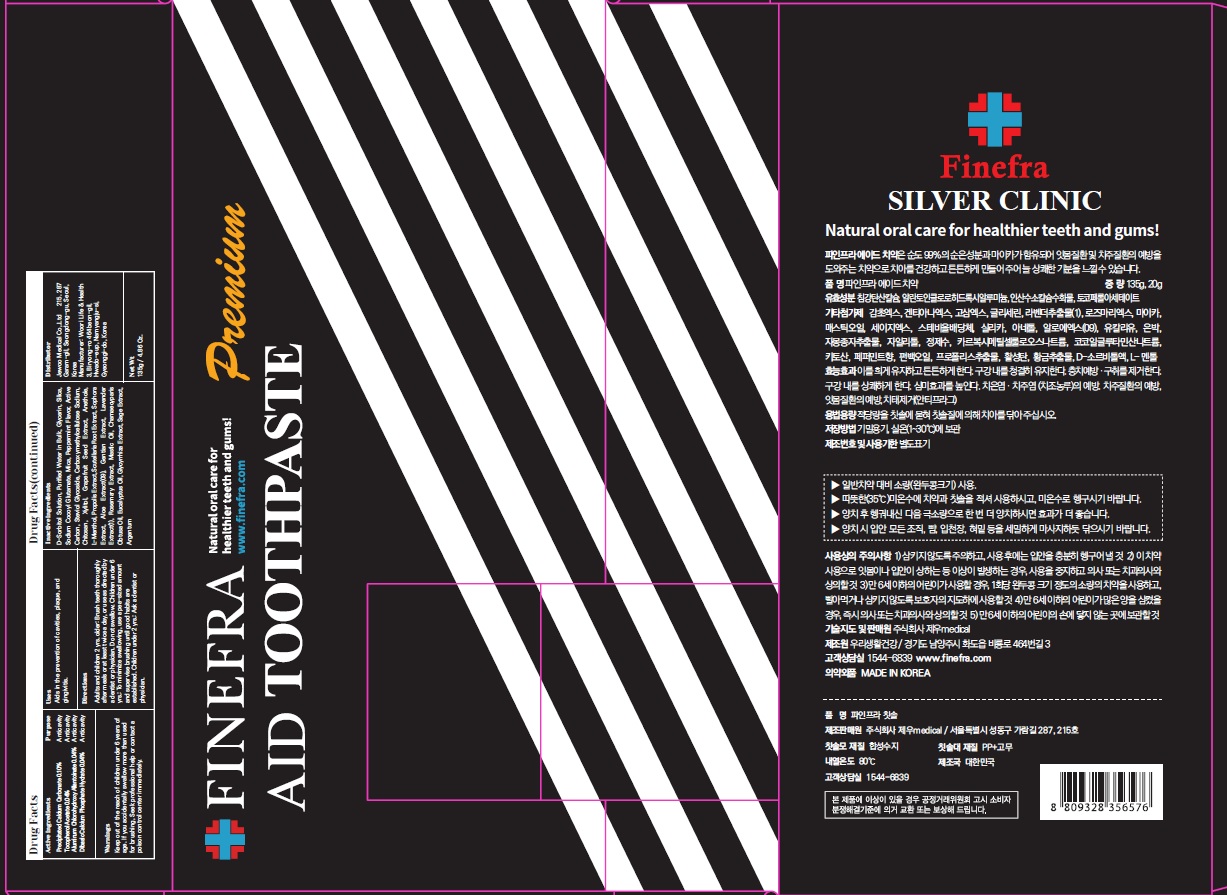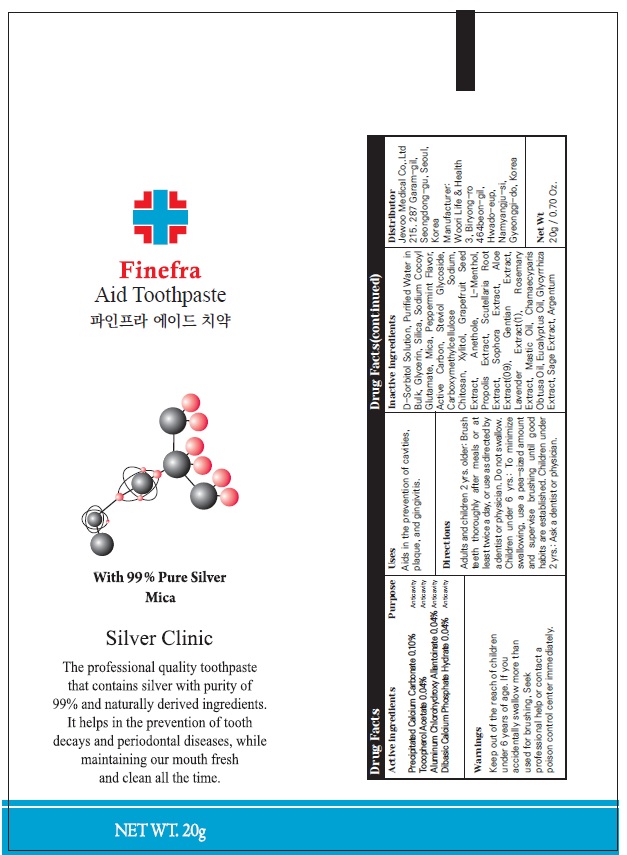 DRUG LABEL: Finefra Aid Tooth
NDC: 69653-130 | Form: PASTE, DENTIFRICE
Manufacturer: Jewoo Medical Co,.Ltd
Category: otc | Type: HUMAN OTC DRUG LABEL
Date: 20200603

ACTIVE INGREDIENTS: CALCIUM CARBONATE 0.10 g/100 g; .ALPHA.-TOCOPHEROL ACETATE 0.04 g/100 g; ALCLOXA 0.04 g/100 g; DIBASIC CALCIUM PHOSPHATE DIHYDRATE 0.04 g/100 g
INACTIVE INGREDIENTS: SORBITOL; Water; Glycerin

ACTIVE INGREDIENTS

Precipitated Calcium Carbonate 0.10%
Tocopherol Acetate 0.04%
Aluminum Chlorohydroxy Allantoinate 0.04%
Dibasic Calcium Phosphate Hydrate 0.04%

INACTIVE INGREDIENTS

D-Sorbitol Solution, Purified Water in Bulk, Glycerin, Silica, Sodium Cocoyl Glutamate, Mica, Peppermint Flavor, Active Carbon, Steviol Glycoside, Carboxymethylcellulose Sodium, Chitosan, Xylitol, Grapefruit Seed Extract, Anethole, L-Menthol, Propolis Extract, Scutellaria Root Extract, Sophora Extract, Aloe Extract(09), Gentian Extract, Lavender Extract(1), Rosemary Extract, Mastic Oil, Chamaecyparis Obtusa Oil, Eucalyptus Oil, Glycyrrhiza Extract, Sage Extract, Argentum

PURPOSE

Anticavity

WARNINGS

Keep out of the reach of children under 6 years of age.

If you accidentally swallow more than used for brushing, Seek professional help or contact a poison control center immediately

KEEP OUT OF REACH OF CHILDREN

Keep out of the reach of children under 6 years of age.

Uses

Aids in the prevention of cavities, plaque, and gingivitis.

Directions

Adults and children 2 yrs. older: Brush teeth thoroughly after meals or at least twice a day, or use as directed by a dentist or physician. Do not swallow. Children under 6 yrs.: To minimize swallowing, use a pea-sized amount and supervise brushing until good habits are established. Children under 2 yrs.: Ask a dentist or physician.